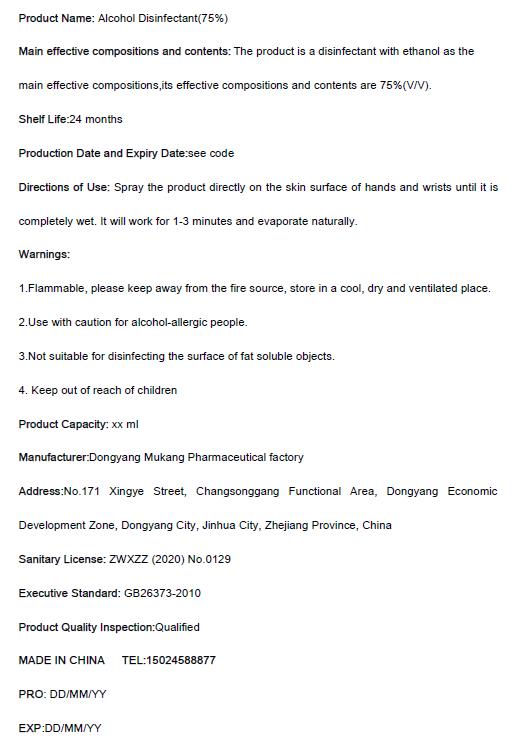 DRUG LABEL: Alcohol Disinfectant (75%)
NDC: 75586-118 | Form: LIQUID
Manufacturer: Dongyang Mukang Pharmaceutical Factory
Category: otc | Type: HUMAN OTC DRUG LABEL
Date: 20200506

ACTIVE INGREDIENTS: ALCOHOL 78 mL/100 mL
INACTIVE INGREDIENTS: WATER

Mukang, Disinfectant, 75% Ethanol, Liquid, xx mL

Active Ingredient(s)

Ethanol 75% v/v. Purpose: Antiseptic

Purpose

Hand sanitizer to help decrease bacteria skin.

Use

Spray the product directly on the skin surface of hands and wrists until it is completely wet. It will work for 1-3 minutes and evaporate naturally.

Warnings

1. Flammable, please keep away from the fire source, store in a cool, dry and ventilated place.
2. Use with caution for alcohol-allergic people.
3. Not suitable for disinfecting the surface of fat soluble objects.
4. Keep out of reach of children.

Do not use

1. Use with caution for alcohol-allergic people.

2. Not suitable for disinfecting the surface of fat soluble objects.

WHEN USING

This product is for external use, no taken orally, avoid contact with eyes.

STOP USE

If there is skin irritation, please stop using. If further irritation, please consult a doctor and keep it below.

Keep away from reach of children.

Directions

Spray the product directly on the skin surface of hands and wrists until it is completely wet. It will work for 1-3 minutes and evaporate naturally.

Other information

Store at a cool place, avoid sunlight.

Inactive ingredients

Purified water.